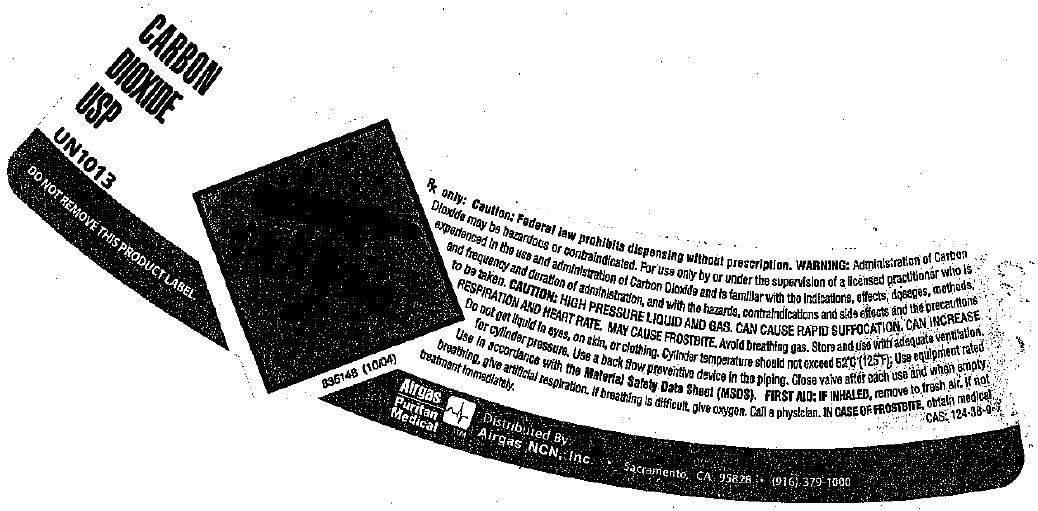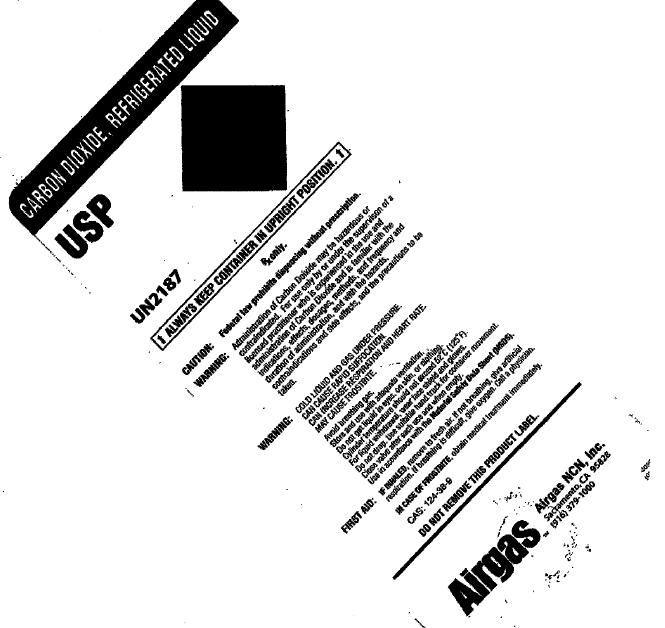 DRUG LABEL: Carbon Dioxide
NDC: 58789-003 | Form: GAS
Manufacturer: Airgas Northern California and Nevada, Inc.
Category: prescription | Type: HUMAN PRESCRIPTION DRUG LABEL
Date: 20100430

ACTIVE INGREDIENTS: Carbon Dioxide 992 mL/1 L

carbon dioxide

PACKAGE LABEL

Carbon Dioxide USP
UN 1013
DO NOT REMOVE THIS PRODUCT LABEL
Rx Only: Caution: Federal law prohibits dispensing without prescription. WARNING: Administration of Carbon Dioxide may hazardous or contraindicated. For use only by or under the supervision of a licensed practitioner who is experienced in the administration of Carbon Dioxide and is familiar with the indications, effects, dosages, methods, and frequency and duration of administration, and with the hazards, and contraindications, and side effects, and the precautions to be taken. CAUTION: HIGH PRESSURE LIQUID AND GAS. CAN CAUSE RAPID SUFFOCATION. CAN INCREASE RESPIRATION AND HEART RATE. MAY CAUSE FROSTBITE. Avoid breathing gas. Store and use with adequate ventilation. Do not get liquid in eyes, on skin, or clothing. Cylinder temperature should not exceed 52 C(125F). Use equipment rated for cylinder pressure. Use a back flow preventive device in the piping. Close valve after each use and when empty. Use in accordance with the Material Safety Data Sheet (MSDS). FIRST AID: IF INHALED, remove to fresh air. If not breathing, give artificial respiration. If breathing is difficult, give oxygen. Call a physician. IN CASE OF FROSTBITE obtain medical treatment immediately. CAS 124-38-9
Airgas Puritan Medical Distributed by Airgas NCN, Inc. Sacramento, CA 95828 (916) 379-1000
835148 (10/04)

PACKAGE LABEL

CARBON DIOXIDE , REFRIGERATED LIQUID USP
UN 2187
ALWAYS KEEP CONTAINER IN UPRIGHT POSITION
Rx Only.
CAUTION: Federal law prohibits dispensing without a prescription.
WARNING: Administration of Carbon Dioxide may hazardous or contraindicated. For use only by or under the supervision of a licensed practitioner who is experienced in the use and administration of Carbon Dioxide and is familiar with the indications, effects, dosages, methods, and frequency and duration of administration, and with the hazards, and contraindications, and side effects, and the precautions to be taken.
WARNING: COLD LIQUID AND GAS UNDER PRESSURE. CAN CAUSE RAPID SUFFOCATION. CAN INCREASE RESPIRATION AND HEART RATE. CAN CAUSE FROSTBITE.
Avoid breathing gas. Store and use with adequate ventilation. Do not get liquid in eyes, on skin or clothing. Cylinder temperature should not exceed 52 C(125F). For liquid withdrawal, wear face shield and gloves. Do not drop. Use suitable hand truck for container movement. Close valve after each use and when empty. Use in accordance with Material Safety Data Sheets (MSDS).
FIRST AID: IF INHALED, remove to fresh air. If not breathing give artificial respiration. If breathing is difficult, give oxygen. Call a physician. IN CASE OF FROSTBITE, obtain medical treatment immediately.
CAS 124-38-9 DO NOT REMOVE THIS PRODUCT LABEL.
Airgas tm Airgas NCN, INC. Sacramento, CA 95828 (916) 379-1000